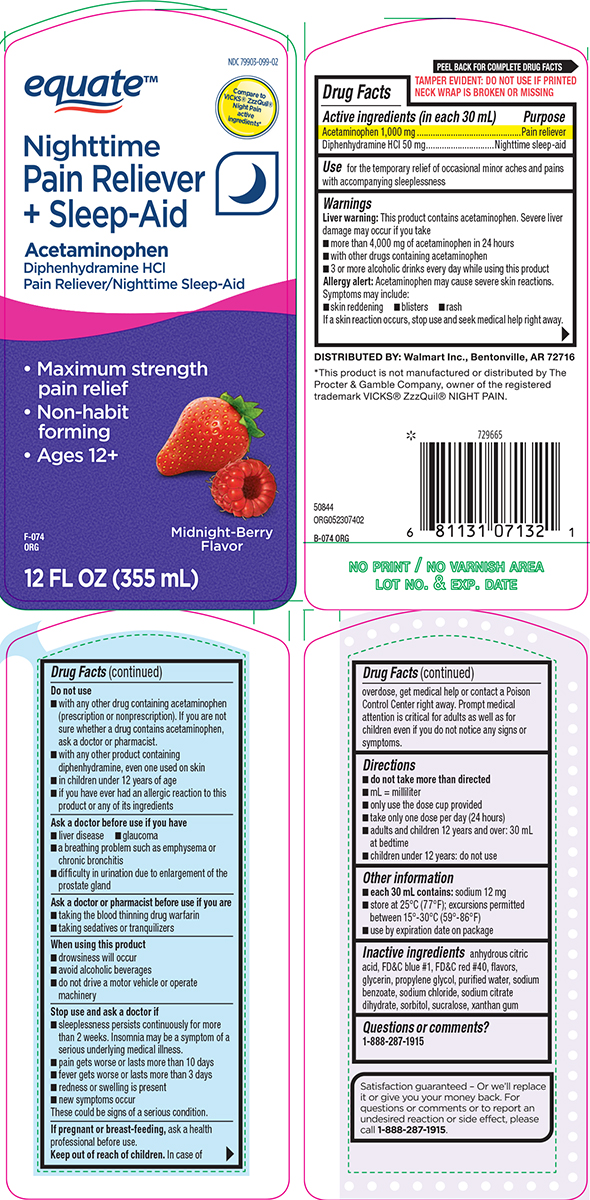 DRUG LABEL: Nighttime Pain Reliever plus Sleep Aid
NDC: 79903-099 | Form: SOLUTION
Manufacturer: WALMART INC.
Category: otc | Type: HUMAN OTC DRUG LABEL
Date: 20260202

ACTIVE INGREDIENTS: ACETAMINOPHEN 1000 mg/30 mL; DIPHENHYDRAMINE HYDROCHLORIDE 50 mg/30 mL
INACTIVE INGREDIENTS: ANHYDROUS CITRIC ACID; FD&C BLUE NO. 1; FD&C RED NO. 40; GLYCERIN; PROPYLENE GLYCOL; WATER; SODIUM BENZOATE; SODIUM CHLORIDE; TRISODIUM CITRATE DIHYDRATE; SORBITOL; SUCRALOSE; XANTHAN GUM

Equate 44-074

Active ingredients (in each 30 mL)

Acetaminophen 1,000 mg
Diphenhydramine HCl 50 mg

Purpose

Pain reliever
Nighttime sleep-aid

Use

for the temporary relief of occasional minor aches and pains with accompanying sleeplessness

Warnings

Liver warning: This product contains acetaminophen. Severe liver damage may occur if you take

- more than 4,000 mg of acetaminophen in 24 hours
- with other drugs containing acetaminophen
- 3 or more alcoholic drinks every day while using this product

Allergy alert: Acetaminophen may cause severe skin reactions. Symptoms may include:

- skin reddening
- blisters
- rash

If a skin reaction occurs, stop use and seek medical help right away.

Do not use

- with any other drug containing acetaminophen (prescription or nonprescription). If you are not sure whether a drug contains acetaminophen, ask a doctor or pharmacist.
- with any other product containing diphenhydramine, even one used on skin
- in children under 12 years of age
- if you have ever had an allergic reaction to this product or any of its ingredients

Ask a doctor before use if you have

- liver disease
- glaucoma
- a breathing problem such as emphysema or chronic bronchitis
- difficulty in urination due to enlargement of the prostate gland

Ask a doctor or pharmacist before use if you are

- taking the blood thinning drug warfarin
- taking sedatives or tranquilizers

When using this product

- drowsiness will occur
- avoid alcoholic beverages
- do not drive a motor vehicle or operate machinery

Stop use and ask a doctor if

- sleeplessness persists continuously for more than 2 weeks. Insomnia may be a symptom of a serious underlying medical illness.
- pain gets worse or lasts more than 10 days
- fever gets worse or lasts more than 3 days
- redness or swelling is present
- new symptoms occur

These could be signs of a serious condition.

If pregnant or breast-feeding,

ask a health professional before use.

Keep out of reach of children.

In case of overdose, get medical help or contact a Poison Control Center right away. Prompt medical attention is critical for adults as well as for children even if you do not notice any signs or symptoms

Directions

- do not take more than directed
- mL = milliliter
- only use the dose cup provided
- take only one dose per day (24 hours)
- adults and children 12 years and over: 30 mL at bedtime
- children under 12 years: do not use

Other information

- each 30 mL contains: sodium 12 mg
- store at 25°C (77°F); excursions permitted between 15°-30°C (59°-86°F)
- use by expiration date on package

Inactive ingredients

anhydrous citric acid, FD&C blue #1, FD&C red #40, flavors, glycerin, propylene glycol, purified water, sodium benzoate, sodium chloride, sodium citrate dihydrate, sorbitol, sucralose, xanthan gum

Questions or comments?

1-888-287-1915

Principal display panel

equate™

NDC 79903-099-02

Compare to
VICKS® ZzzQuil®
Night Pain
active
ingredients*

Nighttime
Pain Reliever
+ Sleep-Aid

Acetaminophen
Diphenhydramine HCl
Pain Reliever/Nighttime Sleep-Aid

• Maximum Strength
pain relief
• Non-habit
forming
• Ages 12+

Midnight-Berry
Flavor

12 FL OZ (355 mL)

TAMPER EVIDENT: DO NOT USE IF PRINTED
NECK WRAP IS BROKEN OR MISSING

Satisfaction Guaranteed- Or we'll replace
it or give you your money back. For
questions or comments or to report an
undesired reaction or side effect, please
call 1-888-287-1915.

DISTRIBUTED BY: Walmart Inc., Bentonville, AR 72716

*This product is not manufactured or distributed by The
Procter & Gamble Company, owner of the registered
trademark VICKS® ZzzQuil® NIGHT PAIN.

50844

ORG052307402

Equate 44-074